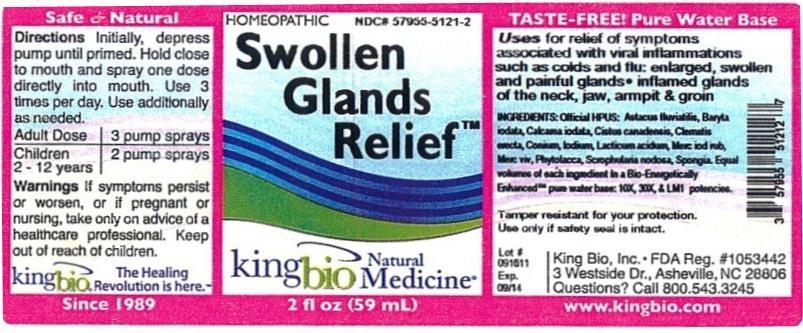 DRUG LABEL: Swollen Glands Relief
NDC: 57955-5121 | Form: LIQUID
Manufacturer: King Bio Inc.
Category: homeopathic | Type: HUMAN OTC DRUG LABEL
Date: 20120712

ACTIVE INGREDIENTS: ASTACUS ASTACUS 10 [hp_X]/59 mL; BARIUM IODIDE 10 [hp_X]/59 mL; CALCIUM IODIDE 10 [hp_X]/59 mL; HELIANTHEMUM CANADENSE 10 [hp_X]/59 mL; CLEMATIS RECTA FLOWERING TOP 10 [hp_X]/59 mL; CONIINE 10 [hp_X]/59 mL; IODINE 10 [hp_X]/59 mL; LACTIC ACID, DL- 10 [hp_X]/59 mL; MERCURIC IODIDE 10 [hp_X]/59 mL; MERCURY 10 [hp_X]/59 mL; PHYTOLACCA AMERICANA ROOT 10 [hp_X]/59 mL; SCROPHULARIA NODOSA 10 [hp_X]/59 mL; SPONGIA OFFICINALIS SKELETON, ROASTED 10 [hp_X]/59 mL
INACTIVE INGREDIENTS: WATER

Swollen Glands Relief

Active Ingredients

Official HPUS: Astacus fluviatilis, Baryta iodata, Calcarea iodata, Cistus Canadensis, Clematis erecta, Coniinum, Iodium, Lacticum acidum, Mercurius iodatus ruber, Mercurius vivus, Phytolacca decandra, Scrophularia nodosa, Spongia tosta

Reference swollen glands relief.jpg

Inactive Ingredient

Equal volumes of each ingredient in a Bio-energetically Enhanced pure water base: 10X, 30X, and LM1 potencies.

Reference swollen glands relief.jpg

Purpose

Uses for relief of symptoms associated with viral inflammations such as colds and flu:

- enlarged, swollen and painful glands
- inflamed glands of the neck, jaw, armpit and groin

Reference image swollen glands relief.jpg

Dosage and Administration

Directions initially, depress pump until primed. Hold close to mouth and spray one dose directly into mouth. Use 3 times per day. Use additionally as needed.

Adult Dose 3 pump sprays

Children 2-12 years 2 pump sprays

Reference image swollen glands relief.jpg

Warnings

If symptoms persist or worsen, or if pregnant or nursing, take only on advice of a healthcare professional. Keep out of reach of children.

Other: Tamper resistant for your protection. Use only if safety seal is intact.

Reference image swollen glands relief.jpg

Keep out of reach of children.

Reference image swollen glands relief.jpg

Indications and usage

Uses for relief of symptoms associated with viral inflammations such as colds and flu, enlarged, swollen and painful glands, inflamed glands of the neck, jaw, armpit and groin.

Reference image swollen glands relief.jpg

PACKAGE LABEL

King Bio, Inc.

3 Westside Drive

Asheville, NC 28806

Question? Call 800.543.3245

wwwkingbio.com

Reference image swollen glands relief.jpg